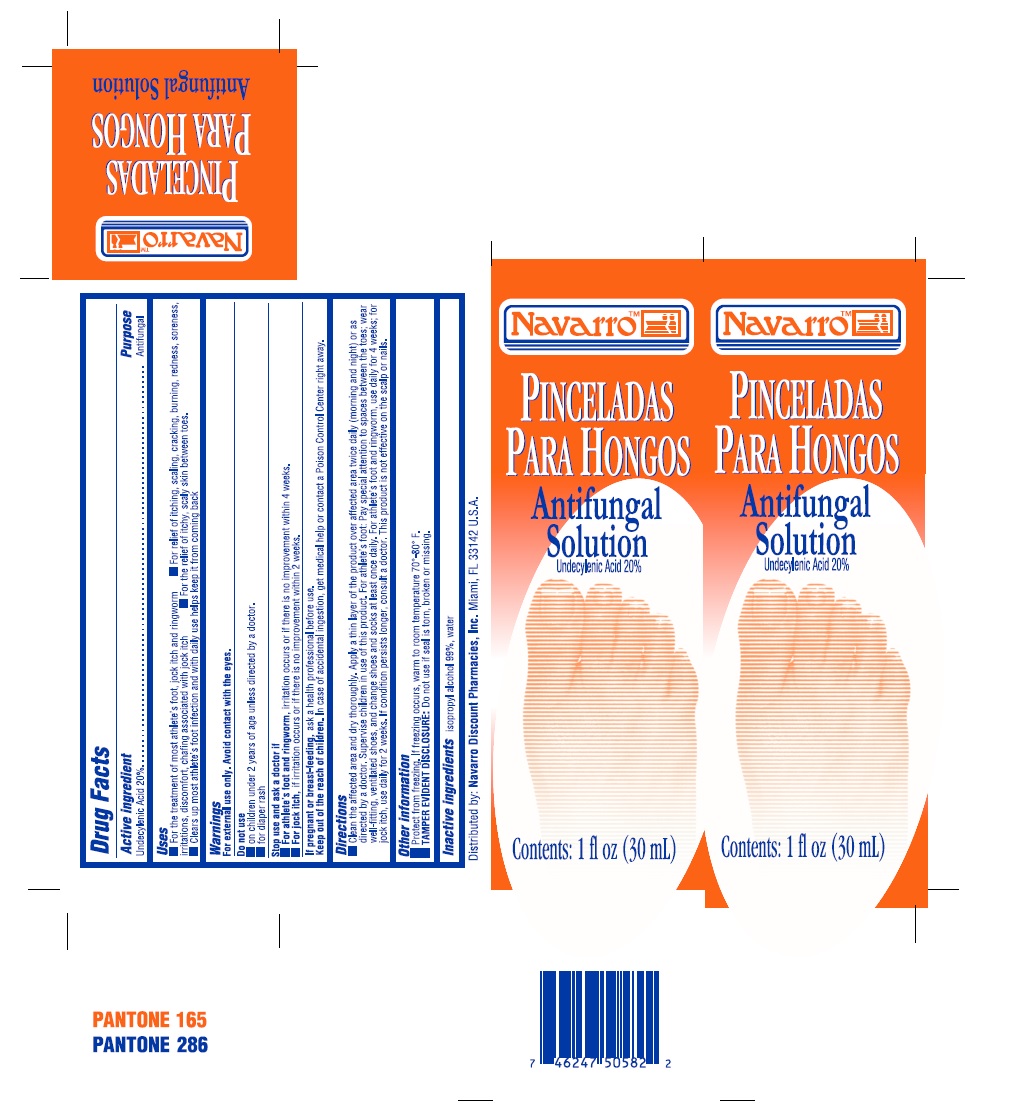 DRUG LABEL: Pinceladas Para Hongos Navarro
NDC: 53145-119 | Form: LIQUID
Manufacturer: Menper Distributors, Inc.
Category: otc | Type: HUMAN OTC DRUG LABEL
Date: 20220218

ACTIVE INGREDIENTS: UNDECYLENIC ACID 200 mg/1 mL
INACTIVE INGREDIENTS: ISOPROPYL ALCOHOL; WATER

Active ingredient

Undecylenic Acid 20%.................Antifungal

Purpose

Antifungal

Uses

- For the treatment of most athelete's foot, jock itch and ringworm
- For relief if itching, scaling, cracking, burning, redness, soreness, irritations, discomfort, chafing associated with jock itch
- For the relief of itch, scaly skin between toes
- Clears up most athelete's foot infection and with daily use helps keep it from comming back

Warnings

For external use only. Avoid contact with the eyes.

Do not use

- on children under 2 years of age unless directed by a doctor.
- for diaper rash

Stop use and ask doctor if

- For athelete's foot and ringworm, irritation occurs or if there is no improvement within 4 weeks.
- For jock itch, if irritation occurs or if there is no improvement within 2 weeks.

If pregnant or breast-feeding,

ask health professional before use.

Keep out of reach of children.

In case of accidental ingestion, get medical help or contact a Poison Control Center right away.

Directions

Clean the affected area and dry thoroughly. Apply a thin layer of the product over affected area twice daily (morning and night) or as directed by a doctor. Supervise children in use of this product. For athelete's foot: Pay special attention to spaces between the toes; wear well-fitting, ventilated shoes, and change shoes and socks at least once daily. For athelete's foot and ringworm, use daily for 4 weeks; for jock itch, use daily for 2 weeks. If condition persists longer, consult a doctor. This product is not effective on the scalp or nails.

Other information

- Protect from freezing. If freezing occurs, warm to room temperature 70°-80° F.
- TAMPER EVIDENT DISCLOSURE: Do not use if seal is torn, broken or missing.

Inactive ingredients

- isopropyl alcohol 99%, water